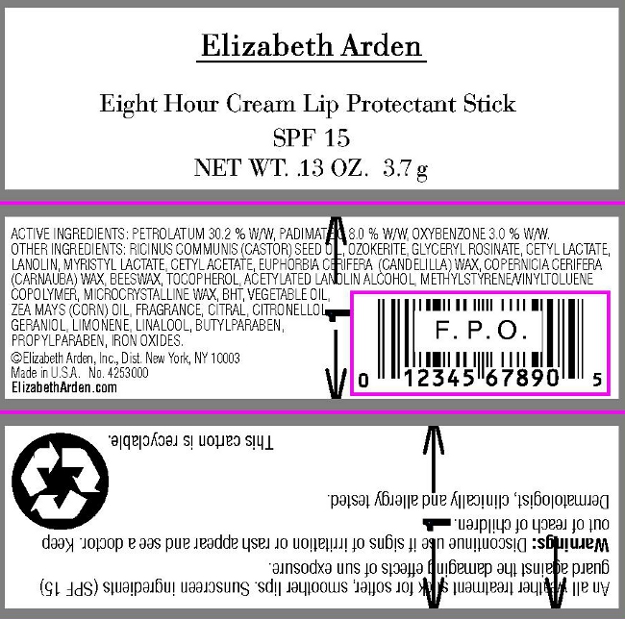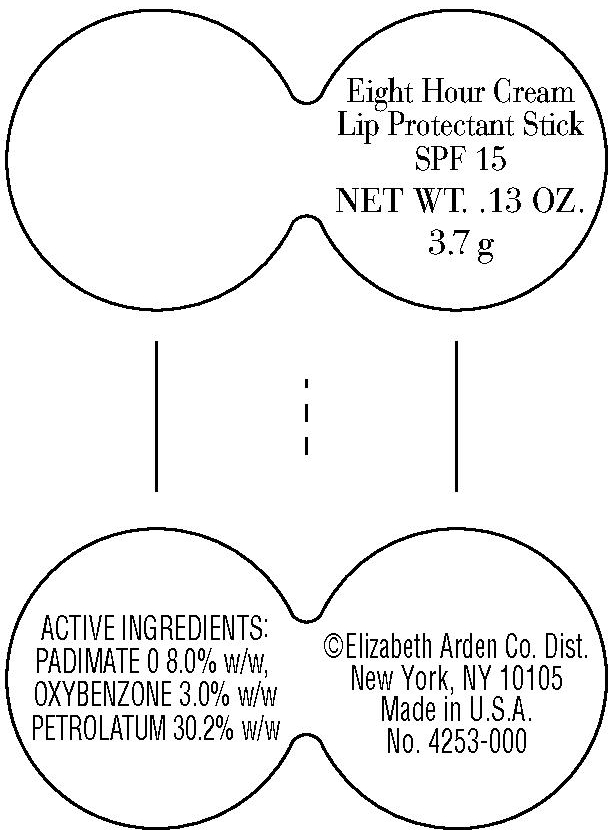 DRUG LABEL: Eight Hour Cream Lip Protectant SPF 15
NDC: 67938-0774 | Form: STICK
Manufacturer: Elizabeth Arden, Inc
Category: otc | Type: HUMAN OTC DRUG LABEL
Date: 20110114

ACTIVE INGREDIENTS: PETROLATUM 1.12 g/3.7 g; PADIMATE O 0.296 g/3.7 g; OXYBENZONE 0.111 g/3.7 g
INACTIVE INGREDIENTS: CASTOR OIL; MYRISTYL LACTATE; OXYBENZONE; CANDELILLA WAX; YELLOW WAX; MICROCRYSTALLINE WAX; PROPYLPARABEN; BUTYLPARABEN; CORN OIL; ALPHA-TOCOPHEROL; BUTYLATED HYDROXYTOLUENE

BL0774

DESCRIPTION

An all weather treatment stick for softer, smoother lips. Sunscreen ingredients (SPF 15) guard against the damaging effects of sun exposure. Dermatologist, clinically and allergy tested.

INDICATIONS AND USAGE

Apply to lips.

WARNINGS

Warnings: Discontinue use if signs of irritation or rash appear and see a doctor. Keep out of reach of children.

OTC - ACTIVE INGREDIENT

Active Ingredients: Petrolatum 30.2% w/w, Padimate O 8.0% w/w, Oxybenzone 3.0% w/w.

INACTIVE INGREDIENT

Other Ingredients: Ricinus Communis (Castor) Seed Oil, Ozokerite, Glyceryl Rosinate, Cetyl Lactate, Myristyl Lactate, Lanolin Oil, Cetyl Acetate, Euphorbia Cerifera (Candelilla) Wax/Candelilla Cera/Cire de Candelilla, Copernicia Cerifera (Carnauba) Wax/Cera Carnauba/Cire De Carnauba, Beeswax/Cera Alba/Cire D'Abeille, Tocopherol, Acetylated Lanolin Alcohol, Methylstyrene/Vinyltoluene Copolymer, Microcrystalline Wax/Cera Microcristallina/Cire Microcristalline, BHT, Vegetable Oil/Olus/Huille Vegetale, Zea Mays (Corn) Oil, Parfum/Fragrance, Citral, Citronellol, Geraniol, Limonene, Linalool, Butylparaben, Propylparaben, Iron Oxides.

DOSAGE & ADMINISTRATION

Apply to lips.

OTC - KEEP OUT OF REACH OF CHILDREN

Keep out of reach of children.

OTC - PURPOSE

Protects skin. Provides SPF 15 sun protection.

OTC - WHEN USING

Discontinue use if signs of irritation or rash appear.